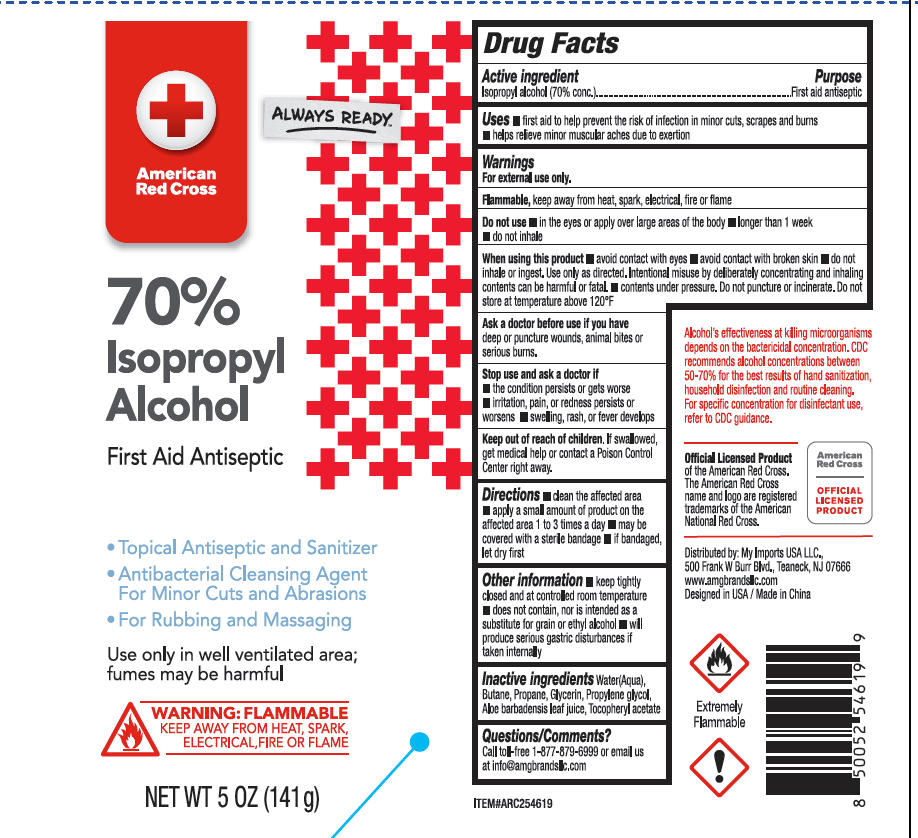 DRUG LABEL: American Red Cross 70% Isopropyl Alcohol
NDC: 51628-4526 | Form: SPRAY
Manufacturer: MY IMPORTS USA LLC
Category: otc | Type: HUMAN OTC DRUG LABEL
Date: 20251027

ACTIVE INGREDIENTS: ISOPROPYL ALCOHOL 70 g/100 g
INACTIVE INGREDIENTS: WATER; BUTANE; PROPYLENE GLYCOL; .ALPHA.-TOCOPHEROL ACETATE; GLYCERIN; ALOE BARBADENSIS LEAF JUICE; PROPANE

American Red Cross 70% Isopropyl Alcohol

Active ingredient

Isopropyl alcohol (70% conc.)

Purpose

First aid antiseptic

Uses

- first aid to help prevent the risk of infection in minor cuts, scrapes and burns
- helps relieve minor muscular aches due to exertion

Warnings

For external use only

Flammable, keep away from heat, spark, electrical, fire or flame.

Do not use

- in the eyes or apply over large areas of the body
- longer than 1 week
- do not inhale

When using this product

- avoid contact with eyes
- avoid contact with broken skin
- do not inhale or ingest. Use only as directed. Interntional misuse by deliberatebly concentrating and inhaling contents can be harmful or fatal.
- contents under pressure. Do not puncture or incinerate. Do not store at temperature above 120 ºF.

Ask a doctor before use if you have deep or puncture wounds, animal bites or serious burns.

Stop use and ask a doctor if

- the condition persists or gets worse
- irritation, pain, or redness persists or worsens
- swelling, rash, or fever develops

Keep out of reach of children

If swallowed, get medical help or contact a Poison Control Center right away.

Directions

- clean the affected area
- apply a small amount of product on the affected area 1 to 3 times a day
- may be covered with a sterile bandage
- if bandaged, let dry first.

Other information

- keep tightly closed and at controlled room temperature
- does not contain, nor is intended as a subsitute for grain or ethyl alcohol
- will produce serious gastric disturbances if taken internally.

Inactive ingredients

Water(Aqua)

Butane

Propane

Glycerin

Propylene glycol

Aloe barbadensis leaf juice

Tocopheryl acetate